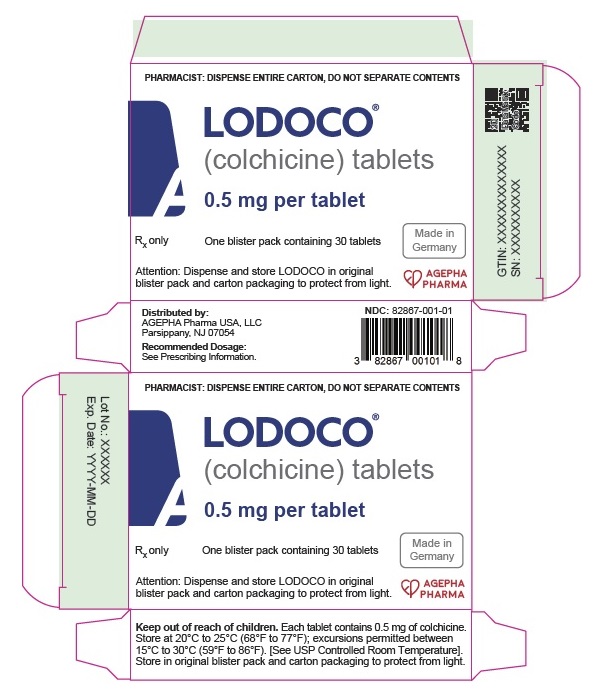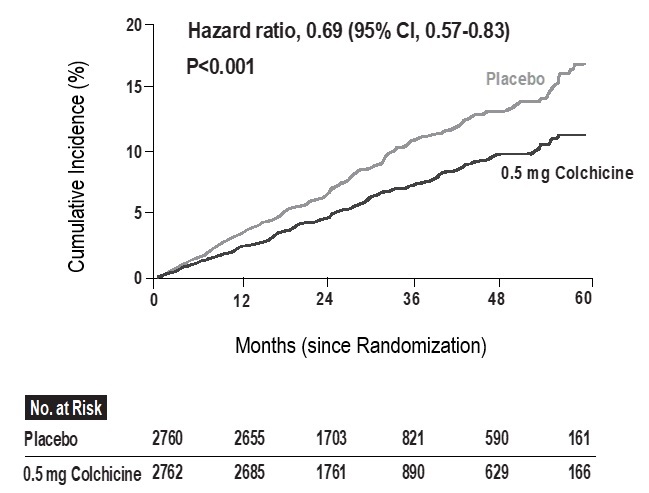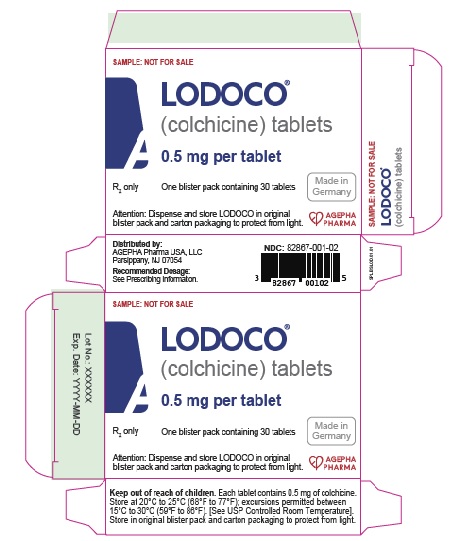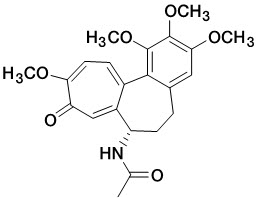 DRUG LABEL: LODOCO
NDC: 82867-001 | Form: TABLET
Manufacturer: AGEPHA Pharma USA, LLC
Category: prescription | Type: HUMAN PRESCRIPTION DRUG LABEL
Date: 20260113

ACTIVE INGREDIENTS: COLCHICINE 0.5 mg/1 1

HIGHLIGHTS OF PRESCRIBING INFORMATION

These highlights do not include all the information needed to use LODOCO safely and effectively. See full prescribing information for LODOCO.
LODOCO (colchicine) tablets, for oral use
Initial U.S. Approval: 1961

1. INDICATION AND USAGE

LODOCO is an alkaloid indicated:
• to reduce the risk of myocardial infarction (MI), stroke, coronary revascularization, and cardiovascular death in adult patients with established atherosclerotic disease or with multiple risk factors for cardiovascular disease (1).

2. DOSAGE AND ADMINISTRATION

The recommended dosage is 0.5 mg orally once daily (2.1).

3. DOSAGE FORMS AND STRENGTHS

Tablets: 0.5 mg (3).

4. CONTRAINDICATIONS

• Concurrent use of strong CYP3A4 inhibitors or P-gp inhibitors with LODOCO is contraindicated, including in patients with hepatic or renal impairment (4).
• LODOCO is contraindicated in patients with pre-existing blood dyscrasias, renal failure, and severe hepatic impairment (4).

5. WARNINGS AND PRECAUTIONS

• Blood dyscrasias: myelosuppression, leukopenia, granulocytopenia, thrombocytopenia, pancytopenia, and aplastic anemia have been reported (5.1).
• Neuromuscular toxicity: Myotoxicity including rhabdomyolysis may occur, especially in combination with other drugs known to cause this effect. Consider temporary interruption or discontinuation of LODOCO (5.2).

6. ADVERSE REACTIONS

The common side-effects reported in published clinical studies and literature with the use of colchicine are gastrointestinal symptoms (diarrhea; vomiting; abdominal cramping) and myalgia (6).

To report SUSPECTED ADVERSE REACTIONS, contact AGEPHA Pharma FZ LLC at 1 (800) 963-0353 or FDA at 1-800-FDA-1088 or www.fda.gov/medwatch.

7. DRUG INTERACTIONS

Coadministration of P-gp and/or CYP3A4 inhibitors (e.g., cyclosporine or clarithromycin) have been demonstrated to alter the concentration of colchicine. The potential for drug-drug interactions must be considered prior to and during therapy. See FPI for a complete list of reported and potential interactions (7).

8. USE IN SPECIFIC POPULATIONS

• Females and Males of Reproductive Potential: Advise males that LODOCO may rarely and transiently impair fertility (8.3).
• Patients with renal or hepatic impairment should be monitored closely for adverse effects of colchicine (8.6, 8.7).

FULL PRESCRIBING INFORMATION

1. INDICATION AND USAGE

LODOCO is indicated to reduce the risk of myocardial infarction (MI), stroke, coronary revascularization, and cardiovascular death in adult patients with established atherosclerotic disease or with multiple risk factors for cardiovascular disease.

2. DOSAGE AND ADMINISTRATION

2.1 Recommended Dosage

The recommended dosage is 0.5 mg orally once daily.

If a dose of LODOCO is missed, the missed dose should be taken as soon as possible, and the patient should then return to the normal dosing schedule. If a dose is skipped, the patient should not double the next dose.

3. DOSAGE FORMS AND STRENGTHS

Tablets: 0.5 mg - White to slightly yellow, round, biconvex tablets, debossed with ‘L1’ on one side and plain on the other side.

4. CONTRAINDICATIONS

- Concurrent use of strong CYP3A4 inhibitors or P-glycoprotein inhibitors with LODOCO is contraindicated, because life-threatening and fatal colchicine toxicity has been reported in these patients with colchicine taken in therapeutic doses [see Drug interactions (7)].

- LODOCO use is contraindicated in patients with renal failure (Creatinine clearance less than 15 mL/minute) and severe hepatic impairment.

- LODOCO is contraindicated in patients with pre-existing blood dyscrasias and in patients hypersensitive to this drug or any inactive ingredient of LODOCO [see Description (11)].

5. WARNINGS AND PRECAUTIONS

5.1 Blood Dyscrasias

LODOCO can cause myelosuppression, leukopenia, granulocytopenia, thrombocytopenia, pancytopenia, and aplastic anemia, which can be life-threatening or fatal [see Adverse Reactions (6)]. Gastrointestinal symptoms often are the first sign of colchicine toxicity, so new symptoms should prompt an evaluation for toxicity. Concomitant use of drugs that reduce the metabolism of colchicine or the presence of hepatic or renal impairment increases the risk of developing blood dyscrasias.

Use of LODOCO in patients with pre-existing blood dyscrasias, renal failure (Creatinine clearance less than 15 mL/minute), or severe hepatic dysfunction, and concomitant use of strong CYP3A4 inhibitors or P-glycoprotein inhibitors is contraindicated [see Contraindications (4)].

Concomitant use of moderate CYP3A4 inhibitors with LODOCO should be avoided in patients with risk factors for increased systemic exposure of colchicine. Monitor patients with any degree of renal impairment and hepatic impairment for colchicine toxicity [see Use in Specific Populations (8.6, 8.7)].

5.2 Neuromuscular Toxicity

LODOCO can cause neuromuscular toxicity and rhabdomyolysis. Concomitant use of drugs that reduce the metabolism of colchicine or the presence of hepatic or renal impairment increases the risk of developing neuromuscular toxicity. Gastrointestinal symptoms often are the first sign of colchicine toxicity, so new symptoms should prompt evaluation for toxicity. Use of LODOCO in patients with renal failure (Creatinine clearance less than 15 mL/minute), or severe hepatic dysfunction, and concomitant use of strong CYP3A4 inhibitors or P-glycoprotein inhibitors is contraindicated [see Contraindications (4)]. Concomitant use of moderate CYP3A4 inhibitors with LODOCO should be avoided in patients with risk factors for increased systemic exposure of colchicine [see Use in Specific Populations (8.6, 8.7) and Drug Interactions (7)].

If a patient develops signs of neuromuscular toxicity, discontinue LODOCO, investigate other causes, and treat appropriately. Concomitant use of LODOCO and HMG CoA reductase inhibitors, gemfibrozil, and fenofibric acid or cyclosporine may potentiate the development of myopathy [see Drug interactions (7)].

Monitor patients with any degree of renal and hepatic impairment for adverse effects of LODOCO.

6. ADVERSE REACTIONS

6.1 Clinical Trials Experience

Because clinical studies are conducted under widely varying and controlled conditions, adverse reaction rates observed in clinical studies of a drug cannot be directly compared to rates in the clinical studies of another drug and may not predict the rates observed in a broader patient population in clinical practice.

In the LoDoCo2 trial, myalgia was reported for 21.2% of individuals randomized to colchicine and 18.5% of individuals randomized to matching placebo (hazard ratio 1.15, 95%CI 1.01-1.31).

6.2 Postmarketing Experience

The following adverse reactions have been identified with colchicine. Because these reactions are reported voluntarily from a population of uncertain size, it is not always possible to estimate their frequency reliably or establish a causal relationship to drug exposure.

These most often occur with excessive accumulation or overdosage [see Overdosage (10)].
Neuromuscular: myotoxicity, weakness, numbness, paresthesia, rhabdomyolysis.
Gastrointestinal: diarrhea, vomiting, abdominal cramping, abdominal pain.

Renal: acute renal impairment
Dermatology: rashes and alopecia
Hematological: thrombocytopenia, leukopenia, pancytopenia

7. DRUG INTERACTIONS

Colchicine is a substrate for the efflux transporter P-glycoprotein (P-gp). CYP3A4 is the primary enzyme involved in the metabolism of colchicine. If LODOCO is administered with drugs that inhibit P-gp, most of which also inhibit CYP3A4, increased concentrations of colchicine are likely (Table 1).

Table 1: Drug Interactions

Drug class | Outcome/effect | Clinical comment
Strong CYP3A4 Inhibitors†; atazanavir clarithromycin darunavir/ritonavir indinavir itraconazole ketoconazole lopinavir/ritonavir nefazodone nelfinavir ritonavir saquinavir telithromycin tipranavir/ritonavir | Significant increases in colchicine plasma levels [see Clinical Pharmacology (12.3)]. | Concomitant use of LODOCO with strong CYP3A4 inhibitors is contraindicated [see Contraindications (4)].
Moderate CYP3A4 Inhibitors; amprenavir aprepitant diltiazem erythromycin fluconazole, fosamprenavir (prodrug of amprenavir) verapamil | Significant increase in colchicine plasma concentration is anticipated. | Monitor patients receiving moderate CYP3A4 inhibitors for signs of colchicine toxicity. Avoid use in patients with existing renal or hepatic impairment [see Warnings and Precautions (5)].
Grapefruit; grapefruit juice | Grapefruit juice increases exposure to colchicine. | Advise patients to avoid grapefruit or grapefruit juice when taking LODOCO.
P- glycoprotein Inhibitors†; cyclosporine ranolazine | Significant increase in colchicine plasma levels is anticipated with P-gp inhibitors. | Concomitant use of LODOCO with strong P-gp inhibitors is contraindicated [see Contraindications (4)].
HMG-Co A Reductase Inhibitors | Pharmacokinetic and/or pharmacodynamic interaction: the addition of one drug to a stable long term regimen of the other has resulted in myopathy and rhabdomyolysis (including fatality). | Monitor patients for signs or symptoms of muscle pain toxicity.
Other Lipid Lowering drugs; fibrates gemfibrozil | Pharmacokinetic and/or pharmacodynamic interaction: the addition of one drug to a stable long term regimen of the other has resulted in myopathy and rhabdomyolysis (including fatality). | Monitor patients for signs or symptoms of muscle pain toxicity.
Digitalis Glycosides; digoxin | P-gp substrate; rhabdomyolysis has been reported. | Monitor patients for signs or symptoms of muscle pain toxicity.
Oral contraceptives; Ethinyl estradiol and norethindrone (Ortho-Novum 1/35) | In healthy female volunteers given coadministered with 0.6 mg colchicine twice daily, hormone concentrations are not affected [see Clinical Pharmacology (12.3)]. Colchicine can interact with oral contraceptives like norethindrone/ethinyl estradiol and can cause adverse events like diarrhea, nausea, upper abdominal pain, cold sweat etc. | Females using oral contraceptives should be prescribed LODOCO with caution and observed for adverse events.

† Patients with renal or hepatic impairment should not be given LODOCO in conjunction with strong CYP3A4 or P-gp inhibitors [see Contraindications (4)].

8. USE IN SPECIFIC POPULATIONS

8.1 Pregnancy

Risk summary

Available human data from published literature on colchicine use in pregnancy over several decades have not identified any drug associated risks for major birth defects, miscarriage, or adverse maternal or fetal outcomes (see Data). Colchicine crosses the human placenta. Although animal reproduction and developmental studies were not conducted with LODOCO (colchicine), published animal reproduction and development studies indicate that colchicine causes embryofetal toxicity and altered postnatal development at exposures within or above the clinical therapeutic range.
The background risk of major birth defects and miscarriage for the indicated population is unknown. All pregnancies have a background risk of birth defect, loss, or other adverse outcomes. In the U.S. general population, the estimated background risk of major birth defects and miscarriage in clinically recognized pregnancies is 2 to 4% and 15 to 20%, respectively.

Data
Human Data
Available data from published observational studies, case series, and case reports over several decades do not suggest an increased risk for major birth defects or miscarriage in pregnant women with rheumatic diseases (such as rheumatoid arthritis, Behcet’s disease, or Familial Mediterranean fever (FMF)) treated with colchicine at therapeutic doses during pregnancy.
Limitations of these data include the lack of randomization and inability to control for confounders such as underlying maternal disease and maternal use of concomitant medications.

8.2 Lactation

Risk summary

Colchicine is present in human milk (see Data). Adverse events in breastfed infants have not been reported in the published literature after administration of colchicine to lactating women. There are no data on the effects of colchicine on milk production. The developmental and health benefits of breastfeeding should be considered along with the mother’s clinical need for LODOCO and any potential adverse effects on the breastfed infant from LODOCO or from the underlying maternal condition.

Data

Limited published data from case reports and a small lactation study demonstrate colchicine is present in breastmilk. A systematic review of literature reported no adverse effects in 149 breastfed children and advised to reconsider breastfeeding if the infant has diarrhea. In a prospective observational cohort study, no gastrointestinal or other symptoms were reported in 38 colchicine-exposed breastfed infants.

8.3 Females and Males of Reproductive Potential

Infertility
Case reports and epidemiology studies in human male subjects on colchicine therapy indicated that infertility from colchicine is rare and may be reversible.

8.4 Pediatric Use

Safety and effectiveness have not been established in pediatric patients.

8.5 Geriatric Use

The total number of subjects included in the LoDoCo2 study who were 65 and over and 75 and over were 3098 (56.1%). No overall differences in safety or effectiveness were observed between these subjects and younger subjects, and other reported clinical experience has not identified differences in responses between the elderly and younger patients, but greater sensitivity of some older individuals cannot be ruled out.

This drug is known to be substantially excreted by the kidney, and the risk of adverse reactions to this drug may be greater in patients with impaired renal function. Because elderly patients are more likely to have decreased renal function, it may be useful to monitor renal function.

8.6 Renal Impairment

Colchicine is known to be excreted renally. In renally impaired patients, the total clearance of colchicine is significantly reduced. In patients, with renal impairment, elevated plasma concentrations of colchicine were observed, and may lead to the development of colchicine toxicity and adverse reactions like myeloneuropathy characterized by proximal weakness and elevated serum creatinine, and possibly rhabdomyolysis [see Warnings and Precautions (5)].

LODOCO is contraindicated in patients with renal failure (Creatinine clearance less than 15 mL/minute). Patients with renal impairment should be monitored closely for adverse effects of colchicine [see Contraindications (4)].

Avoid use in patients with moderate renal impairment receiving moderate CYP3A4 inhibitors [see Contraindications (4), Warnings and Precautions (5) and Clinical Pharmacology (12.3)].

8.7 Hepatic Impairment

Colchicine is primarily metabolized in liver. The clearance of colchicine may be significantly reduced, and plasma half-life prolonged in patients with chronic hepatic impairment, compared to healthy subjects [see Clinical Pharmacology (12.3)]. In patients with hepatic impairment, monitor closely for adverse reactions with LODOCO. LODOCO use in severe hepatic impairment is contraindicated. Avoid use in patients with any degree of hepatic impairment and receiving strong P-gp inhibitors or strong or moderate CYP3A4 inhibitors [see Contraindications (4) and Clinical Pharmacology (12.3)].

10. OVERDOSAGE

Acute overdose exceeding 0.5 mg/kg (35 mg for a 70 kg average adult) is usually fatal. Fatalities have been reported with as little as 7 mg.

Symptoms: Colchicine poisoning presents in three sequential and usually overlapping phases. The first stage of acute colchicine toxicity typically occurs within 24 hours of ingestion and includes gastrointestinal symptoms such as abdominal pain, nausea, vomiting, and diarrhea, and significant fluid loss, leading to volume depletion. Peripheral leukocytosis may also be seen. The second stage develops 24 to 72 hours after ingestion and is characterized by multi-organ failure. Death is usually a result of respiratory depression and cardiovascular collapse. Recovery may be accompanied by rebound leukocytosis about one week after the initial ingestion.

Treatment: No specific antidote is known. Elimination of toxins by gastric lavage followed by activated charcoal should be attempted within 1-2 hours of ingestion. Colchicine is not effectively removed by hemodialysis.

11. DESCRIPTION

LODOCO contains colchicine, which is an alkaloid chemically described as (S)-N-(5,6,7,9-tetrahydro-1,2,3,10-tetramethoxy-9-oxobenzo[a]heptalen-7-yl)acetamide with a molecular formula of C22H25NO6 and a molecular weight of 399.4 g/mol. The structural formula of colchicine is given below.

Colchicine occurs as white to pale yellow powder, very soluble in water.

LODOCO (colchicine) tablets are supplied for oral administration as white to slightly yellow, round, biconvex tablets debossed with ‘L1’ on one side and plain on the other side containing 0.5 mg of colchicine USP as the active ingredient and the following inactive ingredients: gelatin, lactose monohydrate, magnesium stearate, potato starch, and talc.

12. CLINICAL PHARMACOLOGY

12.1 Mechanism of Action

The mechanism of action of colchicine in the prevention of major cardiovascular events is not understood. However, it is known that colchicine disrupts cytoskeletal functions through inhibition of β-tubulin polymerization into microtubules and consequently prevents the activation, degranulation, and migration of neutrophils. Colchicine may also interfere with the intracellular assembly of the inflammasome complex in neutrophils and monocytes that mediates activation of interleukin-1β. These anti-inflammatory effects are consistent with clinical data demonstrating that colchicine reduces high sensitivity C- reactive protein (hs-CRP).

12.2 Pharmacodynamics
The pharmacodynamics of colchicine in the intended indication is not completely understood.

12.3 Pharmacokinetics
In healthy adults, colchicine exhibits linear pharmacokinetics within a dose range of 0.5 to 1.5 mg.
Mean pharmacokinetic parameter values of LODOCO in healthy adults are shown in table 2.

Table 2: Summary of LODOCO Pharmacokinetic Parameters in Healthy Adults under Fasting and Fed Conditions

BE studies | Cmax; ng/ml | Tmax*; hours | t½; hours | AUC0-t; ng·h/ml
Single dose of 0.5 mg; (fasting) | 2.1± 1.0 | 1.0; (Range 0.5-2.3) | 31.9 | 18.6± 7.0
Single dose of 0.5 mg (fed) | 1.8± 0.4 | 1.7; (Range 0.7- 3.5) | 31.0 | 16.4 ± 4.4

*Median and range are presented

Absorption
Oral colchicine intake undergoes an entero-hepatic recirculation. In healthy adults, LODOCO is absorbed when given orally, reaching a mean Cmax 2.1 ng/ml in approximately 1 hour after a single dose administered under fasting conditions.

The mean absolute bioavailability of colchicine is reported to be approximately 45%.

Effect of food
When LODOCO was administered with or following a high-fat, high-calorie meal in a bioavailability study, the results showed a lack of a significant food effect, see Table 2, above. LODOCO may be administered with or without food.
The mean peak plasma concentration of LODOCO under fed conditions was found to be 1.8 ng/ml in approximately 1.75 hour.

Distribution

The mean apparent volume of distribution in healthy volunteers is approximately 1300 L.

Colchicine binding to serum protein is 39 ± 5%, primarily to albumin regardless of concentration. After reabsorption, is rapidly removed from the plasma and distributed to various tissues. Colchicine is found in high concentrations in leucocytes, kidneys, the liver, and spleen.

Colchicine crosses the placenta. Colchicine also distributes into breast milk. Colchicine can also cross the blood-brain barrier and accumulate within the brain, which contains large amount of tubulin [see Use in Specific Populations (8.1, 8.2)].

Elimination

Metabolism

Colchicine is demethylated to two primary metabolites, 2-O-demethylcolchicine and 3-O-demethylcolchicine (2- and 3-DMC, respectively) and one minor metabolite, 10-O-demethylcolchicine (also known as colchiceine). In vitro studies using human liver microsomes have shown that CYP3A4 is involved in the metabolism of colchicine to 2- and 3-DMC. Plasma levels of these metabolites are (less than 5% of parent drug).

Excretion

In healthy volunteers (n=12), 40 to 65% of 1 mg orally administered colchicine was recovered unchanged in urine. Enterohepatic recirculation and biliary excretion are also postulated to play a role in colchicine elimination. Following single oral dose of 0.5 mg daily, the mean effective half-life in healthy volunteers is 19 hours. Colchicine is a substrate of P-gp.
Colchicine is not removed by hemodialysis.

Specific Populations

Geriatric Patients

The pharmacokinetic studies of LODOCO were not conducted in elderly patients. In a study, conducted to compare the relative bioavailability in between 18 elderly subjects and 20 young subjects, the following pharmacokinetic parameter values (mean ± SD) were observed for colchicine in the young and elderly subjects, respectively: AUC (ng/.hr/mL) 22.4 ± 7.0 and 25.0 ± 6.9; Cmax (ng/mL) 2.6 ± 0.7 and 2.6 ± 1.0; Tmax (h) 1.4 ± 0.4 and 1.3 ± 0.4; apparent elimination half-life (h) 24.9 ± 5.3 and 30.1 ± 10.8. No statistical difference in the pharmacokinetic parameters were found between the groups and it was concluded that no dosing adjustments were required in elderly patients.

Another study illustrated that after IV administration of 0.5 mg colchicine to six healthy male adults and 1mg colchicine to four elderly group the absorption is similar in healthy volunteers and elderly subjects. However, a 31 percent decrease in volume of distribution at steady state (2.9 vs 4.2 L/kg) and 48 percent decrease in total body clearance (5.5 vs 10.5 L/h) was seen in elderly patients when compared to healthy volunteers.

Pediatric Patients

The sponsor did not conduct any pharmacokinetic studies in pediatric patients. No literature was found in the database on pharmacokinetics of colchicine in pediatric patients with the intended indication.

Patients with Renal Impairment

The exposure of colchicine was similar for normal renal function and mild impairment (24.7–27.2 ng.h/mL) but doubled in subjects with moderate or severe renal impairment (48.9 and 48.0 ng.h/mL, respectively). The same study showed an unexpected result that subjects with ESRD, prior to and during hemodialysis, only have a modest increase in exposure to colchicine (30.6 – 31.7 ng.h/mL) compared to healthy control. The reason for this is not clear. A small amount of the colchicine dose (mean of 5.2 %) was recovered in dialysate [see Use in Specific Population (8.6)]. In another study, subjects with end-stage renal disease requiring dialysis had 75% lower colchicine clearance (0.17 vs 0.73 L/hr/kg) and prolonged plasma elimination half-life (18.8 vs 4.4 hours) as compared to subjects with normal renal function.

Patients with Hepatic Impairment

From the published literature, in some subjects with mild to moderate cirrhosis, healthy subjects had a mean clearance of 10.7 ml/min.kg, whereas cirrhotic patients had a mean clearance of 4.2 ml/min.kg. The mean half-life was about 57 minutes in control subjects vs. about 114 minutes in cirrhotic patients. Volume of distribution was not different in the two groups (0.7 ± 0.1 L/kg in control subjects; 0.7 ± 0.2 L/kg in cirrhotic patients). The study concluded that cirrhosis impairs colchicine clearance. No pharmacokinetic data are available for patients with severe hepatic impairment [see Use in Specific Population (8.7)].

Drug Interaction Studies

In vitro drug interactions:
In vitro studies in human liver microsomes have shown that colchicine is not an inhibitor or inducer of CYP1A2, CYP2A6, CYP2B6, CYP2C8, CYP2C9, CYP2C19, CYP2D6, CYP2E1, or CYP3A4 activity.

In vivo drug interactions:

The effects of co-administration of other drugs with LODOCO on Cmax, AUC, and Cmin are summarized in Table 3 (effect of other drugs on colchicine). For information regarding clinical recommendations, see Table 1 [see Drug interactions (7)].

Table 3: Effect of other drugs on colchicine pharmacokinetics

Co-administered drug | Dose of Co-administered drug | Dose of Colchicine | Mean pharmacokinetic parameters (%CV) substrate drug |  |  |  | % Change in Colchicine; Concentrations from Baseline; (Range: Min - Max)
Co-administered drug | Dose of Co-administered drug | Dose of Colchicine | Cmax (ng/ml) | AUC0-t; (ng/; hour/; ml) | T1/2 (hours) | Cl/F; (L/; hour) | Cmax | AUC0-t
Cyclosporine | 100 mg OD | 0.6 mg, single dose | 2.7 | 12.6 | 6.8 | 48.2 | 270; (62 to 606.9) | 259; (75.8 to 511.9)
Clarithromycin | 250 mg BID | 0.6 mg, single dose | 2.8 | 12.4 | 8.9 | 46.8 | 227.2 (65.7 to 591.1) | 281.5 (88.7 to 851.6)
Ketoconazole | 200 mg BID | 0.6 mg, single dose | 2.8 | 12.0 | 6.3 | 49.3 | 101.7 (19.6 to 219) | 212.2; (76.7 to 419.6)
Ritonavir | 100 mg BID | 0.6 mg, single dose | 1.9 | 8.4 | 5.2 | 67.9 | 184.4; (79.2 to 447.4) | 296; (53.8 to 924.4)
Verapamil | 240 mg OD | 0.6 mg, single dose | 3.0 | 13.1 | 4.3 | 43.9 | 40.1; (-47.1 to 149.5) | 103.3; (-9.8 to 217.2)
Diltiazem | 240 mg OD | 0.6 mg, single dose | 2.2 | 10.0 | 5.5 | 58.9 | 44.2; (-46 to 318.3) | 93.4; (-30.2 to 338.6)
Azithromycin | 500 mg OD | 0.6 mg, single dose | 2.7 | 12.0 | 6.1 | 50.2 | 21.6; (-41.7 to 222) | 57.1 (-24.3 to 241.1)
Atorvastatin | 40 mg OD | 0.6 mg, single dose | 2.5 | 10.7 | 4.3 | 58.6 | 130.60; (111.1-153.5) | 127.3; (109.1–148.7)
Grapefruit juice | 240 mL twice daily, 4 days | 0.6 mg, single dose | - | - | - | - | -2.6; (-53.4 to 55.0) | -2.4; (-4.6 to 62.2)

Estrogen-containing oral contraceptives: In healthy female volunteers given ethinyl estradiol and norethindrone (Ortho-Novum 1/35) co-administered with colchicine 0.6 mg b.i.d. × 14 days, hormone concentrations are not affected.

13. NONCLINICAL TOXICOLOGY

13.1 Carcinogenesis, Mutagenesis, Impairment of Fertility

Carcinogenesis

Two-year studies were conducted in mice and rats to assess the carcinogenic potential of colchicine. No evidence of colchicine-related tumorigenicity was observed in mice or rats at colchicine oral doses up to 3 and 2 mg/kg/day, respectively, approximately 29 and 38 times, the recommended human dose of 0.5 mg on a mg/m^2 basis.

Mutagenesis

Colchicine was negative for mutagenicity in the bacterial reverse mutation assay. In a chromosomal aberration assay in cultured human white blood cells, colchicine treatment resulted in the formation of micronuclei. Since published studies demonstrated that colchicine induces aneuploidy from the process of mitotic nondisjunction without structural DNA changes, colchicine is not considered clastogenic, although micronuclei are formed.

Impairment of Fertility

No studies of colchicine effects on fertility were conducted with LODOCO. However, published nonclinical studies demonstrated that colchicine-induced disruption of microtubule formation affects meiosis and mitosis. Reproductive studies also reported abnormal sperm morphology and reduced sperm counts in males, and interference with sperm penetration, second meiotic division and normal cleavage in females when exposed to colchicine. Colchicine administered to pregnant animals resulted in fetal death and teratogenicity. These effects were dose-dependent, with the timing of exposure critical for the effects on embryofetal development. The nonclinical doses evaluated were generally higher than an equivalent human therapeutic dose, but safety margins for reproductive and developmental toxicity could not be determined.

14. CLINICAL STUDIES

The evidence for the efficacy of colchicine in patients with cardiovascular events is derived from published literature (LoDoCo2) along with other supportive studies.
The LoDoCo2 trial was an investigator-initiated, randomized, placebo controlled, double-blind, event-driven trial conducted to assess the efficacy of colchicine 0.5mg once daily orally in patients with stable coronary artery disease. The study included 5522 patients, in which 2762 were assigned to the colchicine group and 2760 to placebo. The baseline characteristics of the patients were balanced between the trial groups. Patients were treated for chronic coronary disease, with 99.7% taking an antiplatelet agent or an anticoagulant, 96.6% a lipid-lowering agent, 97.3% of which were statins, 62.1% a beta-blocker, and 71.7% an inhibitor of the renin–angiotensin system.
LoDoCo2 assessed the efficacy of colchicine 0.5 mg once daily in patients with stable coronary artery disease. Patients between 35-85 years were eligible for participation in the LoDoCo2 trial if they had proven coronary artery disease, were clinically stable for at least 6 months, without comorbidities that would preclude follow-up, or contraindication to colchicine use. The mean (±SD) age of the patients was 66±8.6 years, and 846 (15.3%) were female. The median time on study medication was 28.6 months. The primary end point of LoDoCo2 trial was a composite of cardiovascular death, spontaneous (nonprocedural) myocardial infarction, ischemic stroke, or ischemia-driven coronary revascularization.

In the LoDoCo2 trial, 0.5 mg of colchicine once daily resulted in a 31% lower relative risk (RRR) of the primary composite endpoint events compared to placebo (HR, 0.69; 95% [CI] 0.57 to 0.83; p<0.001) and the number needed to treat (NNT) was 36.

The results of the primary endpoint are summarized in Table 4.

Table 4: Summary of efficacy results of LoDoCo2 trial

 | LoDoCo2 Trial
End Point | Colchicine (N=2762) No. of patients (%) | Placebo (N=2760) No. of patients (%) | Hazard ratio (95% Cl) | P value
Primary end point Cardiovascular death, myocardial infarction, ischemic stroke, or ischemia driven coronary revascularization | 187 (6.8) | 264 (9.6) | 0.69 (0.57–0.83) | <0.001
Ischemia-driven coronary revascularization | 135 (4.9) | 177 (6.4) | 0.75 (0.60–0.94)
Myocardial infarction | 83 (3.0) | 116 (4.2) | 0.70 (0.53–0.93)
Ischemic stroke | 16 (0.6) | 24 (0.9) | 0.66 (0.35–1.25)
Cardiovascular death | 20 (0.7) | 25 (0.9) | 0.80 (0.44–1.44)

Myocardial infarction refers to spontaneous (non-procedural) myocardial infarction.

16. HOW SUPPLIED/STORAGE AND HANDLING

16.1 How Supplied

LODOCO (colchicine) tablets 0.5 mg are white to slightly yellow, round, and biconvex and debossed with ‘L1’ on one side and plain on the other side and they are available as a single Aluminum/PVC blister pack of 30 tablets, which is secondary packaged in a carton: NDC 82867-001-01.

16.2 Storage

Store LODOCO at 20°C to 25°C (68°F to 77°F); excursions permitted between 15°C to 30°C (59°F to 86°F), [See USP Controlled Room Temperature].

Store LODOCO tablets in the original package in order to protect from light.

17. PATIENT COUNSELING INFORMATION

Advise the patient to read the FDA-approved patient labeling (Patient Information).

Dosing Instructions

- Advise patients to take LODOCO as prescribed, and patients should not alter or discontinue the medication without consulting their healthcare provider.
- Advise patients that if the dose of LODOCO is missed, they should take the missed dose as soon as possible and return to the normal dosing schedule.
- If a dose is skipped advise patient not to double the next dose.

Drug and food interactions

Patients should be advised that many drugs or other substances may interact with LODOCO and some interactions could be fatal. Therefore, patients should report to their healthcare provider all of the current medications they are taking and check with their healthcare provider before starting any new medications, particularly antibiotics. Patients should also be advised to report the use of nonprescription medication or herbal products. Advise patients that grapefruit and grapefruit juice may also interact and should not be consumed during LODOCO treatment.

Colchicine Toxicity

Advise patients that gastrointestinal symptoms are often the first sign of colchicine toxicity. Patients should be instructed to contact their healthcare provider if new symptoms develop.

Neuromuscular Toxicity

Inform patients that muscle pain or weakness, tingling or numbness in fingers or toes may occur with LODOCO alone or when it is used with certain other drugs. Concomitant use of LODOCO and HMG CoA reductase inhibitors, gemfibrozil, and fenofibric acid or cyclosporine may potentiate the development of myopathy (muscles weakness, fatigue). Patients developing any of these signs or symptoms must discontinue LODOCO and seek medical evaluation immediately. Concomitant use of interacting drugs, including statins, or renal or hepatic insufficiency increases the risk of developing toxicity.

Infertility

Advise males of reproductive potential that LODOCO may rarely and transiently impair fertility [see Use in Specific Populations (8.3)].

------------------------------------------------------------------------------------------------------------------------------------------------------------------------------

Distributed by:
AGEPHA Pharma USA, LLC
181 New Road, Suite 304
Parsippany, NJ 07054

PATIENT INFORMATION

LODOCO (Low-Doe-Co)

(colchicine)

tablets, for oral use

What is LODOCO?

LODOCO is a prescription medicine used to reduce the risk of heart attack, stroke, certain types of heart procedures, and cardiovascular death in adults with:

known buildup of plaque inside the arteries (atherosclerotic disease), or

with multiple risk factors for cardiovascular disease.

Do not take LODOCO if you:

take certain medicines called strong CYP3A4 inhibitors or P-glycoprotein inhibitors. Ask your healthcare provider if you are not sure. Taking certain medicines with LODOCO may cause your level of LODOCO to be too high in your body and cause life-threatening side effects or death.
have severe kidney or liver problems.
have blood problems.
are allergic to colchicine or any of the ingredients in LODOCO. See the end of this leaflet for a complete list of ingredients in LODOCO.

Before taking LODOCO, tell your healthcare provider about all your medical conditions, including if you:

have liver or kidney problems.
are pregnant or plan to become pregnant. It is not known if LODOCO will harm your unborn baby.

are breastfeeding or plan to breastfeed. LODOCO can pass into your breast milk. Talk to your healthcare provider about the best way to feed your baby during treatment with LODOCO.

Tell your healthcare provider about all the medicines you take, including prescription and over-the-counter medicines, vitamins, and herbal supplements. Especially tell your healthcare provider if you take:

certain medicines called moderate CYP3A4 inhibitors
cholesterol lowering medicines
cyclosporine

antibiotics

Ask your healthcare provider or pharmacist if you are not sure if you take any of the medicines listed above. This is not a complete list of all the medicines that can interact with LODOCO.

Taking LODOCO with certain other medicines can affect each other and cause serious side effects or death.
Do not start a new medicine without talking to your healthcare provider. Your healthcare provider can tell you if it is safe to take LODOCO with other medicines.

Know the medicines you take. Keep a list of them and show it to your healthcare provider and pharmacist when you get a new medicine.

How should I take LODOCO?

Take LODOCO exactly as your healthcare provider tells you to take it.
Do not change your dose or stop taking LODOCO without talking to your healthcare provider first.
Take LODOCO by mouth 1 time each day.
If you miss a dose of LODOCO, take it as soon you remember and then take your next dose at your regular time. Do not take 2 doses of LODOCO at the same time to make up for a missed dose.

If you take too much LODOCO, go to the nearest hospital emergency room right away.

What should I avoid while taking LODOCO?

Avoid eating grapefruit or drinking grapefruit juice while taking LODOCO. Grapefruit and grapefruit juice may increase your chance of side effects while taking LODOCO.

What are the possible side effects of LODOCO?

LODOCO may cause serious side effects, including:

Blood problems. LODOCO can cause low red blood cell counts, low white blood cell counts, and low platelet counts, which can be life-threatening or may lead to death.

Muscle weakness (neuromuscular toxicity). LODOCO can cause muscle weakness and muscle problems. Stop taking LODOCO and get medical help right away if you get muscle pain or weakness, or tingling or numbness in your fingers or toes.

The most common side effects of LODOCO include:

diarrhea, vomiting, and stomach-area (abdominal) cramping. Tell your healthcare provider right away if you develop any of these symptoms, they are often the first sign of having too much LODOCO in your body.
muscle pain

LODOCO may cause temporary fertility problems in males. This may affect your ability to father a child. Talk to your healthcare provider if this is a concern for you.

Tell your healthcare provider if you have any side effect that is new, that bothers you or that does not go away. These are not all of the possible side effects of LODOCO.

Call your doctor for medical advice about side effects. You may report side effects to FDA at 1-800-FDA-1088.

You may also report side effects to AGEPHA Pharma FZ LLC at 1-800-963-0353.

How should I store LODOCO?

Store LODOCO at room temperature between 68°F to 77°F (20°C to 25°C).
Store LODOCO in the original package in order to protect from light.

Keep LODOCO and all medicines out of the reach of children.

General information about the safe and effective use of LODOCO.

Medicines are sometimes prescribed for purposes other than those listed in a Patient Information leaflet. Do not use LODOCO for a condition for which it was not prescribed. Do not give LODOCO to other people, even if they have the same symptoms that you have. It may harm them. You can ask your pharmacist or healthcare provider for information about LODOCO that is written for health professionals.

What are the ingredients in LODOCO?

Active Ingredient: colchicine.

Inactive Ingredients: gelatin, lactose monohydrate, magnesium stearate, potato starch, and talc.

Distributed by: AGEPHA Pharma USA, LLC, 181 New Road, Suite 304, Parsippany, NJ 07054 For more information, go to www.LODOCO.com or call 1-800-963-0353.

This Patient Information has been approved by the U.S. Food and Drug Administration. Issued: 06/2023